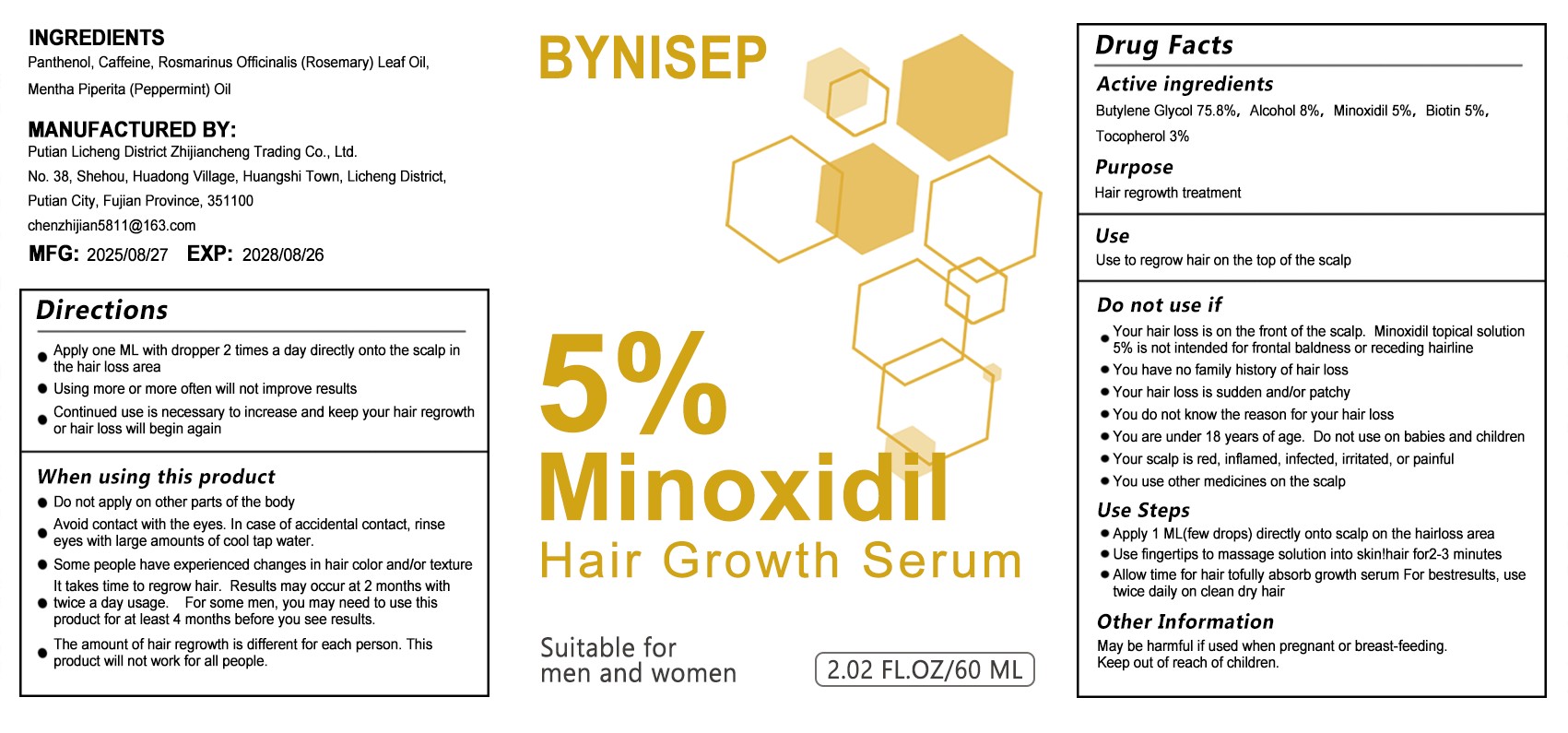 DRUG LABEL: BYNISEP  5% MINOXIDIL HAIR GROWTH SERUM
NDC: 87152-001 | Form: LIQUID
Manufacturer: Putian Licheng District Zhijiancheng Trading Co., Ltd.
Category: otc | Type: HUMAN OTC DRUG LABEL
Date: 20251007

ACTIVE INGREDIENTS: BIOTIN 5 g/100 mL; TOCOPHEROL 3 g/100 mL; MINOXIDIL 5 g/100 mL; ALCOHOL 8 g/100 mL; BUTYLENE GLYCOL 75.8 g/100 mL
INACTIVE INGREDIENTS: PANTHENOL; CAFFEINE; MENTHA PIPERITA (PEPPERMINT) OIL; ROSMARINUS OFFICINALIS (ROSEMARY) LEAF OIL

ACTIVE INGREDIENT

Active ingredientsButylene Glycol 75.8%,Alcohol 8%,Minoxidil 5%,Biotin 5%,Tocopherol 3%

PURPOSE

Hair regrowth treatment

Keep out of Reach of children ,You are under 18 years of age. Do not use on babies and children

Do not use if
Your hair loss is on the front of the scalp. Minoxidil topical solution5% is not intended for frontal baldness or receding hairlineYou have no family history of hair lossYour hair loss is sudden and/or patchye You do not know the reason for your hair lossYou are under 18 years of age. Do not use on babies and childrenYour scalp is red, infamed, infected, irritated, or painfulYou use other medicines on the scalp

INACTIVE INGREDIENT

Panthenol, Caffeine, Rosmarinus Officinalis (Rosemary) Leaf Oil,Mentha Piperita (Peppermint) Oil

DOSAGE AND ADMINISTRATION

Apply 1 ML(few drops) directly onto scalp on the hairloss areaUse fingertips to massage solution into skin!hair for2-3 minuteseAllow time for hair tofully absorb growth serum For bestresults, usetwice daily on clean dry hair

INDICATIONS AND USAGE

Do not apply on other parts of the body
Avoid contact with the eyes. In case of accidental contact, rinseeyes with large amounts of cool tap water.Some people have experienced changes in hair color and/or textureIt takes time to regrow hair. Results may occur at 2 months withtwice a day usage. For some men, you may need to use thisproduct for at least 4 months before you see results.
The amount of hair regrowth is different for each person. Thisproduct will not work for all people.